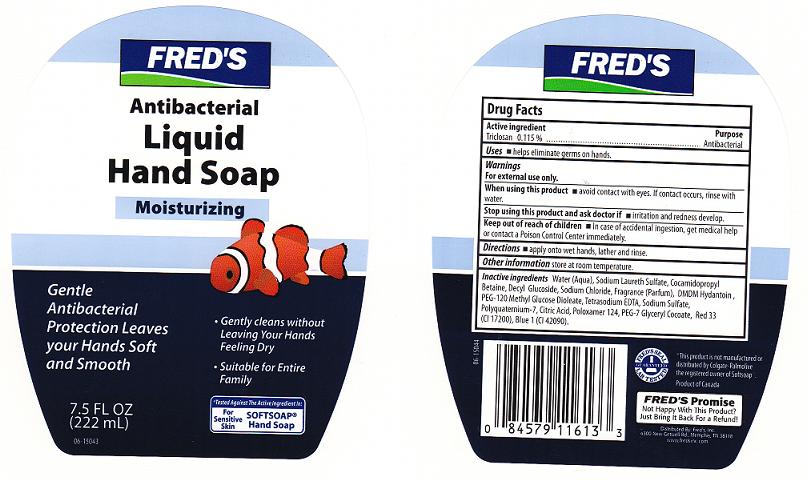 DRUG LABEL: ANTIBACTERIAL 
NDC: 55315-720 | Form: LIQUID
Manufacturer: FRED'S INC
Category: otc | Type: HUMAN OTC DRUG LABEL
Date: 20110726

ACTIVE INGREDIENTS: TRICLOSAN 0.115 mL/100 mL
INACTIVE INGREDIENTS: WATER; SODIUM LAURETH SULFATE; COCAMIDOPROPYL BETAINE; DECYL GLUCOSIDE; POLYQUATERNIUM-7 (70/30 ACRYLAMIDE/DADMAC; 1600 KD); PEG-7 GLYCERYL COCOATE; PEG-120 METHYL GLUCOSE DIOLEATE; EDETATE SODIUM; SODIUM CHLORIDE; DMDM HYDANTOIN; CITRIC ACID MONOHYDRATE; FD&C BLUE NO. 1; D&C RED NO. 33; SODIUM SULFATE; POLOXAMER 124

DRUG FACTS

ACTIVE INGREDIENT

TRICLOSAN 0.115%

PURPOSE

ANTIBACTERIAL

USES

HELPS ELIMINATE GERMS ON HANDS.

WARNINGS

FOR EXTERNAL USE ONLY.

WHEN USING THIS PRODUCT

AVOID CONTACT WITH EYES. IF CONTACT OCCURS, RINSE WITH WATER.

STOP USING THIS PRODUCT AND ASK DOCTOR IF

IRRITATION AND REDNESS DEVELOP.

KEEP OUT OF REACH OF CHILDREN

IN CASE OF ACCIDENTAL INGESTION, GET MEDICAL HELP OR CONTACT A POISON CONTROL CENTER IMMEDIATELY.

DIRECTIONS

APPLY ONTO WET HANDS, LATHER, AND RINSE.

OTHER INFORMATION

STORE AT ROOM TEMPERATURE.

INACTIVE INGREDIENTS

WATER, SODIUM LAURETH SULFATE, COCAMIDOPROPYL BETAINE, DECYL GLUCOSIDE, SODIUM CHLORIDE, FRAGRANCE, DMDM HYDANTOIN, PEG-120 METHYL GLUCOSE DIOLEATE, TETRASODIUM EDTA, SODIUM SULFATE, POLYQUATERNIUM-7, CITRIC ACID, POLOXAMER 124, PEG- 7 GLYCERYL COCOATE, RED 33 (CI 17200), BLUE 1 (CI 42090).